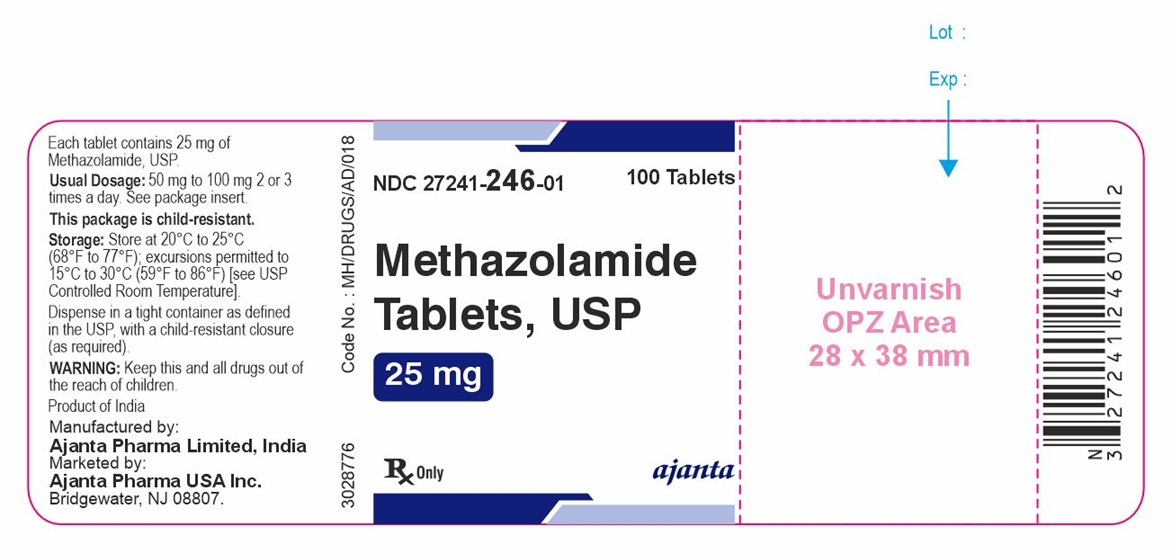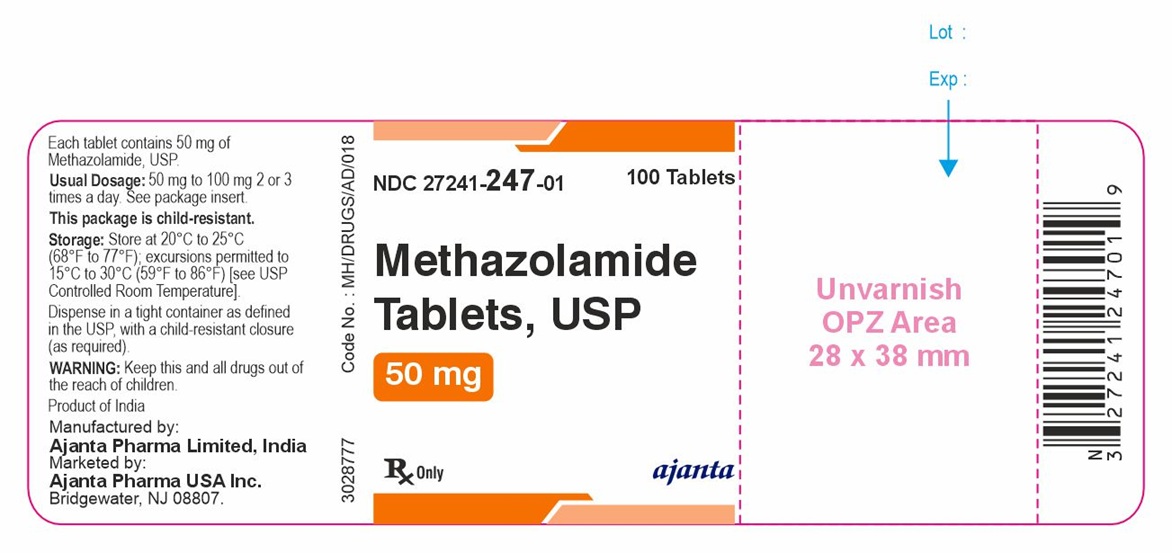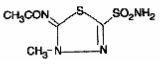 DRUG LABEL: Methazolamide
NDC: 27241-246 | Form: TABLET
Manufacturer: Ajanta Pharma USA Inc.
Category: prescription | Type: Human Prescription Drug Label
Date: 20260210

ACTIVE INGREDIENTS: METHAZOLAMIDE 25 mg/1 1
INACTIVE INGREDIENTS: SILICON DIOXIDE; CROSCARMELLOSE SODIUM; DIBASIC CALCIUM PHOSPHATE DIHYDRATE; MAGNESIUM STEARATE; MICROCRYSTALLINE CELLULOSE

DESCRIPTION

Methazolamide USP, a sulfonamide derivative, is a white or faintly yellow, crystalline powder, weakly acidic, slightly soluble in acetone, very slightly soluble in water and alcohol. The chemical name for methazolamide is: N-[5-(aminosulfonyl)-3-methyl-1,3,4-thiadiazol-2(3H)-ylidene]-acetamide and it has the following structural formula:

C5H8N4O3S2

236.27

Each tablet, for oral administration, contains 25 mg or 50 mg methazolamide USP. In addition, each tablet contains the following inactive ingredients: colloidal silicon dioxide, croscarmellose sodium, dibasic calcium phosphate dihydrate, magnesium stearate (powder), and microcrystalline cellulose.

CLINICAL PHARMACOLOGY

Methazolamide is a potent inhibitor of carbonic anhydrase.

Methazolamide is well absorbed from the gastrointestinal tract. Peak plasma concentrations are observed 1 hour to 2 hours after dosing. In a multiple-dose, pharmacokinetic study, administration of methazolamide 25 mg twice daily, 50 mg twice daily, and 100 mg twice daily demonstrated a linear relationship between plasma methazolamide levels and methazolamide dose. Peak plasma concentrations (Cmax) for the 25 mg, 50 mg and 100 mg twice daily regimens were 2.5 mcg/mL, 5.1 mcg/mL, and 10.7 mcg/mL, respectively. The area under the plasma concentration-time curves (AUC) was 1,130 mcg.min/mL, 2,571 mcg.min/mL, and 5,418 mcg.min/mL for the 25 mg, 50 mg, and 100 mg dosage regimens, respectively.

Methazolamide is distributed throughout the body including the plasma, cerebrospinal fluid, aqueous humor of the eye, red blood cells, bile and extracellular fluid. The mean apparent volume of distribution (Varea/F) ranges from 17 L to 23 L. Approximately 55% is bound to plasma proteins. The steady-state methazolamide red blood cell:plasma ratio varies with dose and was found to be 27:1, 16:1, and 10:1 following the administration of methazolamide 25 mg twice daily, 50 mg twice daily, and 100 mg twice daily, respectively.

The mean steady-state plasma elimination half-life for methazolamide is approximately 14 hours. At steady-state, approximately 25% of the dose is recovered unchanged in the urine over the dosing interval. Renal clearance accounts for 20% to 25% of the total clearance of drug. After repeated twice daily to thrice daily dosing, methazolamide accumulates to steady-state concentrations in 7 days.

Methazolamide’s inhibitory action on carbonic anhydrase decreases the secretion of aqueous humor and results in a decrease in intraocular pressure. The onset of the decrease in intraocular pressure generally occurs within 2 hours to 4 hours, has a peak effect in 6 hours to 8 hours and a total duration of 10 hours to 18 hours.

Methazolamide is a sulfonamide derivative; however, it does not have any clinically significant antimicrobial properties. Although methazolamide achieves a high concentration in the cerebrospinal fluid, it is not considered an effective anticonvulsant.

Methazolamide has a weak and transient diuretic effect; therefore, use results in an increase in urinary volume, with excretion of sodium, potassium, and chloride. The drug should not be used as a diuretic. Inhibition of renal bicarbonate reabsorption produces an alkaline urine. Plasma bicarbonate decreases, and a relative, transient metabolic acidosis may occur due to a disequilibrium in carbon dioxide transport in the red blood cell. Urinary citrate excretion is decreased by approximately 40% after doses of 100 mg every 8 hours. Uric acid output has been shown to decrease 36% in the first 24 hour period.

INDICATIONS AND USAGE

Methazolamide Tablets, USP are indicated in the treatment of ocular conditions where lowering intraocular pressure is likely to be of therapeutic benefit, such as chronic open-angle glaucoma, secondary glaucoma, and preoperatively in acute angle-closure glaucoma where lowering the intraocular pressure is desired before surgery.

CONTRAINDICATIONS

Methazolamide therapy is contraindicated in situations in which sodium and/or potassium serum levels are depressed, in cases of marked kidney or liver disease or dysfunction, in adrenal gland failure, and in hyperchloremic acidosis. In patients with cirrhosis, use may precipitate the development of hepatic encephalopathy.

Long-term administration of methazolamide is contraindicated in patients with angle-closure glaucoma, since organic closure of the angle may occur in spite of lowered intraocular pressure.

WARNINGS

Fatalities have occurred, although rarely, due to severe reactions to sulfonamides including Stevens-Johnson syndrome, toxic epidermal necrolysis, fulminant hepatic necrosis, agranulocytosis, aplastic anemia, and other blood dyscrasias. Hypersensitivity reactions may recur when a sulfonamide is readministered, irrespective of the route of administration.

If hypersensitivity or other serious reactions occur, the use of this drug should be discontinued.

Caution is advised for patients receiving high-dose aspirin and methazolamide concomitantly, as anorexia, tachypnea, lethargy, coma, and death have been reported with concomitant use of high-dose aspirin and carbonic anhydrase inhibitors.

PRECAUTIONS

General

Potassium excretion is increased initially upon administration of methazolamide and in patients with cirrhosis or hepatic insufficiency could precipitate a hepatic coma.

In patients with pulmonary obstruction or emphysema, where alveolar ventilation may be impaired, methazolamide should be used with caution because it may precipitate or aggravate acidosis.

Information for Patients

Adverse reactions common to all sulfonamide derivatives may occur: anaphylaxis, fever, rash (including erythema multiforme, Stevens-Johnson syndrome, toxic epidermal necrolysis), crystalluria, renal calculus, bone marrow depression, thrombocytopenic purpura, hemolytic anemia, leukopenia, pancytopenia, and agranulocytosis. Precaution is advised for early detection of such reactions, and the drug should be discontinued and appropriate therapy instituted.

Caution is advised for patients receiving high-dose aspirin and methazolamide concomitantly.

Laboratory Tests

To monitor for hematologic reactions common to all sulfonamides, it is recommended that a baseline CBC and platelet count be obtained on patients prior to initiating methazolamide therapy and at regular intervals during therapy. If significant changes occur, early discontinuance and institution of appropriate therapy are important. Periodic monitoring of serum electrolytes is also recommended.

Drug Interactions

Methazolamide should be used with caution in patients on steroid therapy because of the potential for developing hypokalemia.

Caution is advised for patients receiving high-dose aspirin and methazolamide concomitantly, as anorexia, tachypnea, lethargy, coma and death have been reported with concomitant use of high-dose aspirin and carbonic anhydrase inhibitors (see WARNINGS).

Carcinogenesis, Mutagenesis, Impairment of Fertility

Long-term studies in animals to evaluate the carcinogenic potential of methazolamide and its effect on fertility have not been conducted. Methazolamide was not mutagenic in the Ames bacterial test.

Pregnancy

Teratogenic effects. Methazolamide has been shown to be teratogenic (skeletal anomalies) in rats when given in doses approximately 40 times the human dose. There are no adequate and well controlled studies in pregnant women. Methazolamide should be used during pregnancy only if the potential benefit justifies the potential risk to the fetus.

Nursing Mothers

It is not known whether this drug is excreted in human milk. Because many drugs are excreted in human milk and because of the potential for serious adverse reactions in nursing infants from methazolamide, a decision should be made whether to discontinue nursing or to discontinue the drug, taking into account the importance of the drug to the mother.

Pediatric Use

The safety and effectiveness of methazolamide in children have not been established.

ADVERSE REACTIONS

Adverse reactions, occurring most often early in therapy, include paresthesias, particularly a “tingling” feeling in the extremities; hearing dysfunction or tinnitus; fatigue; malaise; loss of appetite; taste alteration; gastrointestinal disturbances such as nausea, vomiting, and diarrhea; polyuria; and occasional instances of drowsiness and confusion.

Metabolic acidosis and electrolyte imbalance may occur.

Transient myopia has been reported. This condition invariably subsides upon diminution or discontinuance of the medication.

Other occasional adverse reactions include urticaria, melena, hematuria, glycosuria, hepatic insufficiency, flaccid paralysis, photosensitivity, convulsions, and, rarely, crystalluria and renal calculi. Also see PRECAUTIONS: Information for Patients for possible reactions common to sulfonamide derivatives. Fatalities have occurred, although rarely, due to severe reactions to sulfonamides including Stevens-Johnson syndrome, toxic epidermal necrolysis, fulminant hepatic necrosis, agranulocytosis, aplastic anemia, and other blood dyscrasias (see WARNINGS).

OVERDOSAGE

No data are available regarding methazolamide overdosage in humans as no cases of acute poisoning with this drug have been reported. Animal data suggest that even a high dose of methazolamide is nontoxic. No specific antidote is known. Treatment should be symptomatic and supportive.

Electrolyte imbalance, development of an acidotic state, and central nervous system effects might be expected to occur. Serum electrolyte levels (particularly potassium) and blood pH levels should be monitored.

Supportive measures may be required to restore electrolyte and pH balance.

DOSAGE AND ADMINISTRATION

The effective therapeutic dose administered varies from 50 mg to 100 mg two or three times daily. The drug may be used concomitantly with miotic and osmotic agents.

HOW SUPPLIED

Methazolamide Tablets, USP 25 mg are round, off-white to white, biconvex, uncoated tablets, debossed with “M1” on one side and plain on the other side and are supplied in bottles of 100 with child-resistant closure, NDC 27241-246-01.

Methazolamide Tablets, USP 50 mg are round, off-white to white, flat beveled edged, uncoated scored tablets, debossed with “M2” on one side and break line on the other side and are supplied in bottles of 100 with child-resistant closure, NDC 27241-247-01.

Store at 20°C to 25°C (68°F to 77°F); excursions permitted to 15°C to 30°C (59°F to 86°F) [see USP Controlled Room temperature].

Dispense in a tight container as defined in the USP, with a child-resistant closure (as required).

Rx only

Product of India
Manufactured by:
Ajanta Pharma Limited, India
Marketed by:
Ajanta Pharma USA Inc.
Bridgewater, NJ 08807.
Revised: 02/2026

PACKAGE LABEL.PRINCIPAL DISPLAY PANEL

NDC 27241-246-01

100 Tablets

Methazolamide Tablets, USP

25 mg

Rx Only

ajanta

NDC 27241-247-01

100 Tablets

Methazolamide Tablets, USP

50 mg

Rx Only

ajanta